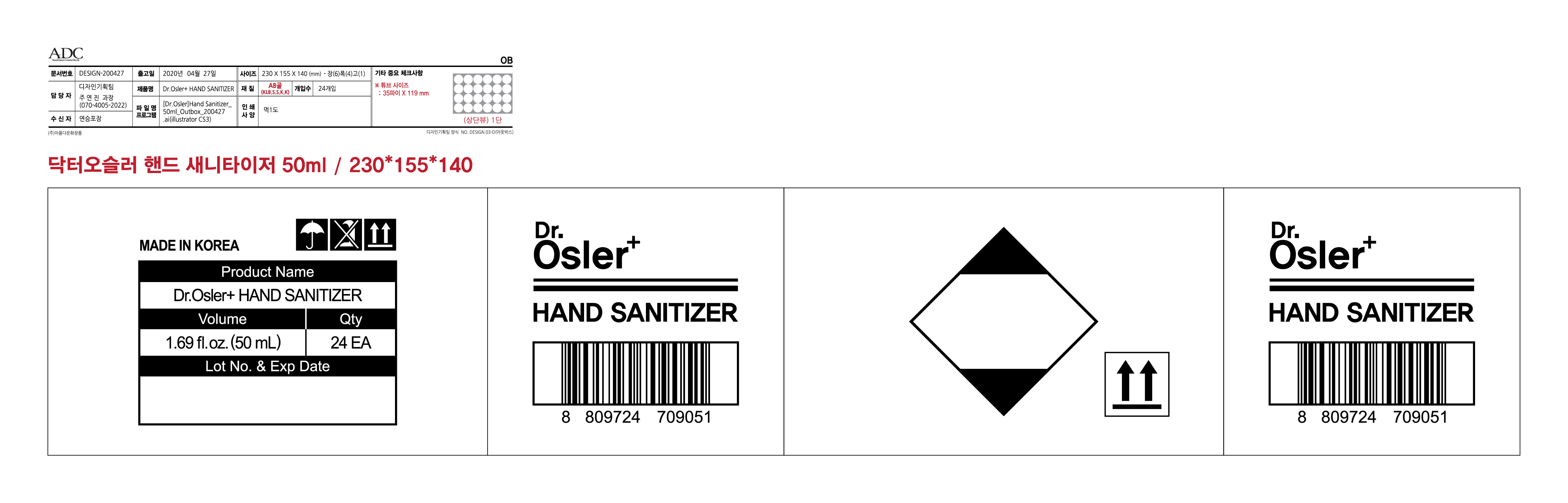 DRUG LABEL: Dr.Osler HAND SANITIZER
NDC: 78050-0002 | Form: GEL
Manufacturer: Corelandmark Inc.
Category: otc | Type: HUMAN OTC DRUG LABEL
Date: 20200603

ACTIVE INGREDIENTS: ALCOHOL 35 mL/50 mL
INACTIVE INGREDIENTS: GLYCERIN; WATER; CARBOMER HOMOPOLYMER, UNSPECIFIED TYPE; ALOE VERA WHOLE

Drug Facts

ACTIVE INGREDIENT

Alcohol

INACTIVE INGREDIENT

Water, Acrylates/C10-30 Alkyl Acrylate Crosspolymer, Butylene Glycol, Triethanolamine, Aloe Barbadensis Leaf Extract, Eucalyptus Globulus Leaf Extract, Glycerin, 1,2-Hexanediol, Ethylhexylglycerin, Carbomer, Fragrance

PURPOSE

Antiseptic

KEEP OUT OF REACH OF THE CHILDREN

INDICATIONS AND USAGE

For the external use only

WARNINGS

For external use only.

Flammable, keep away from fire or flame.

When using this product keep out of eyes. If contact with eyes occurs, rinse promptly and thoroughly with water.

Stop use and ask a doctor if significant irritation or sensitization develops.

Keep out of reach of children. If swallowed, get medical help or contact a Poison Control Center right away.

DOSAGE AND ADMINISTRATION

Put enough amount in your palm and rub hands together until dry. Children under 6 years of age should be supervised by adult who is older than 21 years of age.